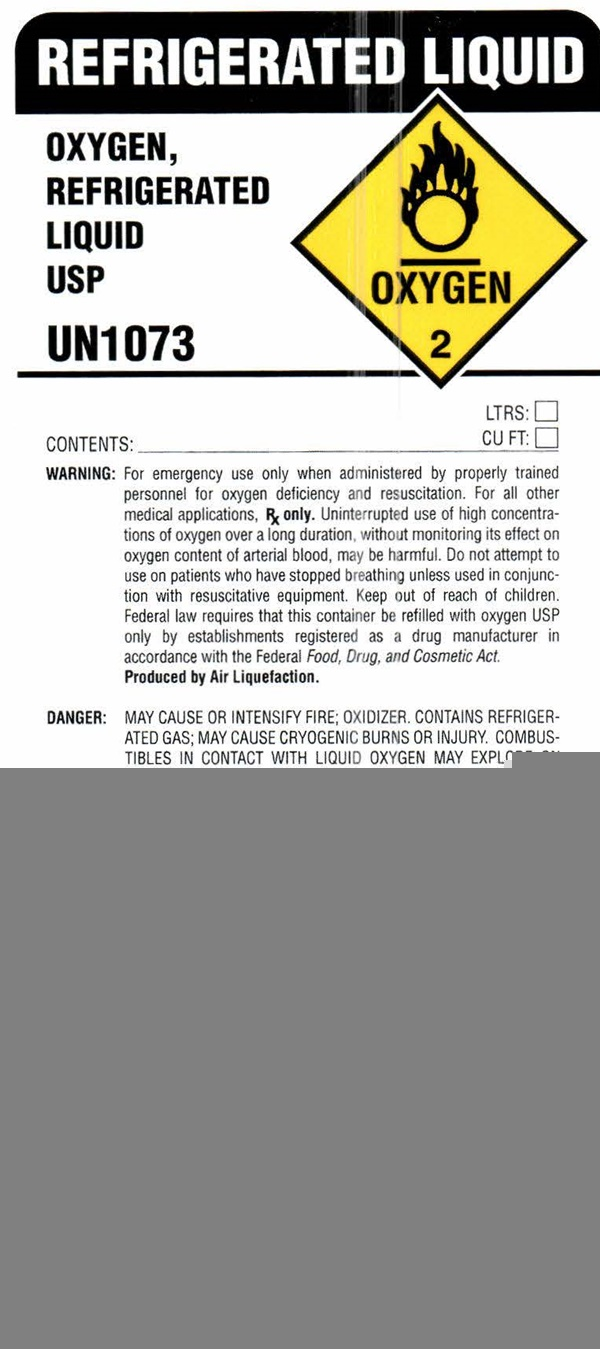 DRUG LABEL: OXYGEN
NDC: 49221-3000 | Form: GAS
Manufacturer: Strate Welding Supply Co., Inc.
Category: prescription | Type: HUMAN PRESCRIPTION DRUG LABEL
Date: 20241028

ACTIVE INGREDIENTS: OXYGEN 99 L/100 L

OXYGEN - 3000

OXYGEN REFRIGERATED LIQUID USP LABEL

REFRIGERATED LIQUID

OXYGEN REFRIGERATED LIQUID USP
OXYGEN 2

UN1073

Contents: _________ LTRS:____________ CU FT:

WARNING: For emergency use only when administered by properly trained personnel for oxygen deficiency and recuscitation. For all other medical applications, Rx only. Uninterrupted use of high concentrations of oxygen over a long duration, without monitoring its errect on oxygen content of arterial blood, may be harmful. do not attempt to use on patients who have stopped breathing unless used in conjunction with resuscitative equipment. Keep out of reach of children. Federal law requires hat this container be refilled with oxygen USP only be establishments registered as a drug manufacture in accordance with theFederal Food, Drug, and Cosmetic Act.

Produced by Air Liquefation.

DANGER: MAY CAUSE OR INTENSIFY FIRE; OXIDIZER. CONTAINS REFRIGERATED GAS; MAY CAUSE CRYOGENIC BURNS OR INJURY. COMBUSTIBLES IN CONTACT WITH LIQUID OXYGEN MAY EXPLODE ON IGNITIONN OR IMPACT. Do not handle until all safety precautions have been read and understood. Keep and store away from clothing and other combustible materials. Keep valves and fittings free from grease and oil. Use and store only outdoors or in a well ventilated place. Wear cold insulating gloves, face shield, and eye protection. in case of fire: Stop leak if safe to do so. Use a back flow preventive device in the piping. Use only with equipment of compatible materials of construction and rated for cylinder pressure. Use only with equipment cleaned for oxygen service. DO NOT change or force fit connections. Avoid spills. Do not walk or roll equipment over spills. Close valve after each use and when empty. Always keep container in upright position. Read and follow the Safety Data Sheet (SDS) before use.

FIRST AID: IF ON SKIN: Thaw frosted parts with lukewarm water. Do not rub affected ared. Get immediate medical advics/attention.

CAS: 7782-44-7

DO NOT REMOVE THIS PRODUCT LABEL

STRATE WELDING SUPPLY CO., INC.

101 COMET STREET • BUFFALO, NY 14216

716-873-3660

47136 (01/15)